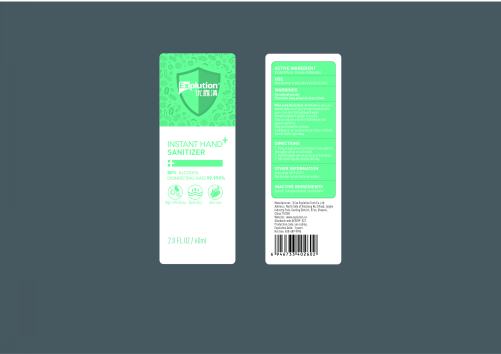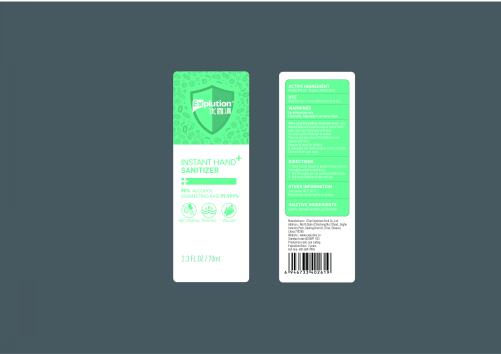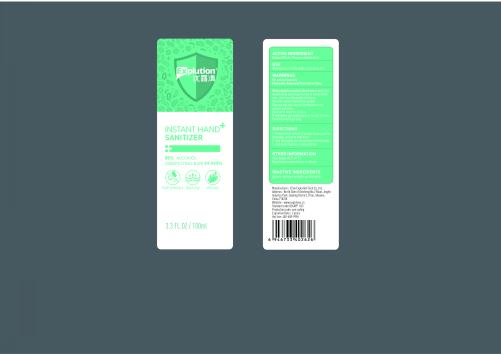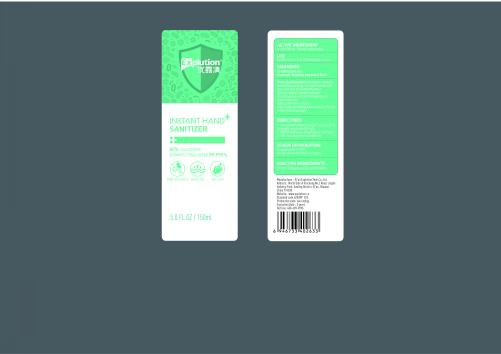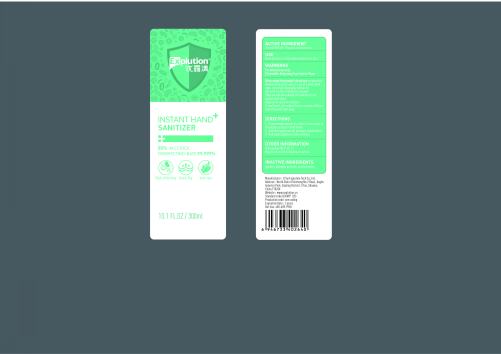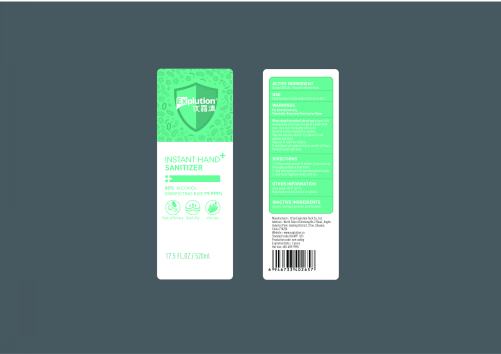 DRUG LABEL: Instant Hand Sanitizer
NDC: 75709-002 | Form: GEL
Manufacturer: Xi'an Explution Tech Co.,Ltd.
Category: otc | Type: HUMAN OTC DRUG LABEL
Date: 20200429

ACTIVE INGREDIENTS: ALCOHOL 80 mL/100 mL
INACTIVE INGREDIENTS: HYDROGEN PEROXIDE; GLYCERIN; WATER

Instant Hand Sanitizer

ACTIVE INGREDIENT

Alcohol 80%v/v.

Purpose

Antimicrobial

USE

Hand Sanitizer to help reduce bacteria on skin.

WARNINGS

For external use only.

Flammable.Keep away from heat or flame.

When using this product

do not use on open skin Wounds.Keep out of eyes.ln.case of contact with eyes.rinse eyes thoroughly with water.

Use with caution if allergic to alcohoL.

Stop use and ask a doctor if irritation of rash appears and tasts.

Keep out of reach for children

If swallowed.get medical help or contact a Poison Control Center right away.

DIRECTIONS

1.Pump enough amount of product in your palm to thoroughly spread on both hands.

2.Rub thoroughly over all surfaces of both hands.

3.Rub hands together briskly until dry.

OTHER INFORMATION

Store below 106°F.(41°C)

May discolor certain fabrics or surface.

INACTIVE INGREDIENTS

glycerin.hydrogen peroxide, purified water.